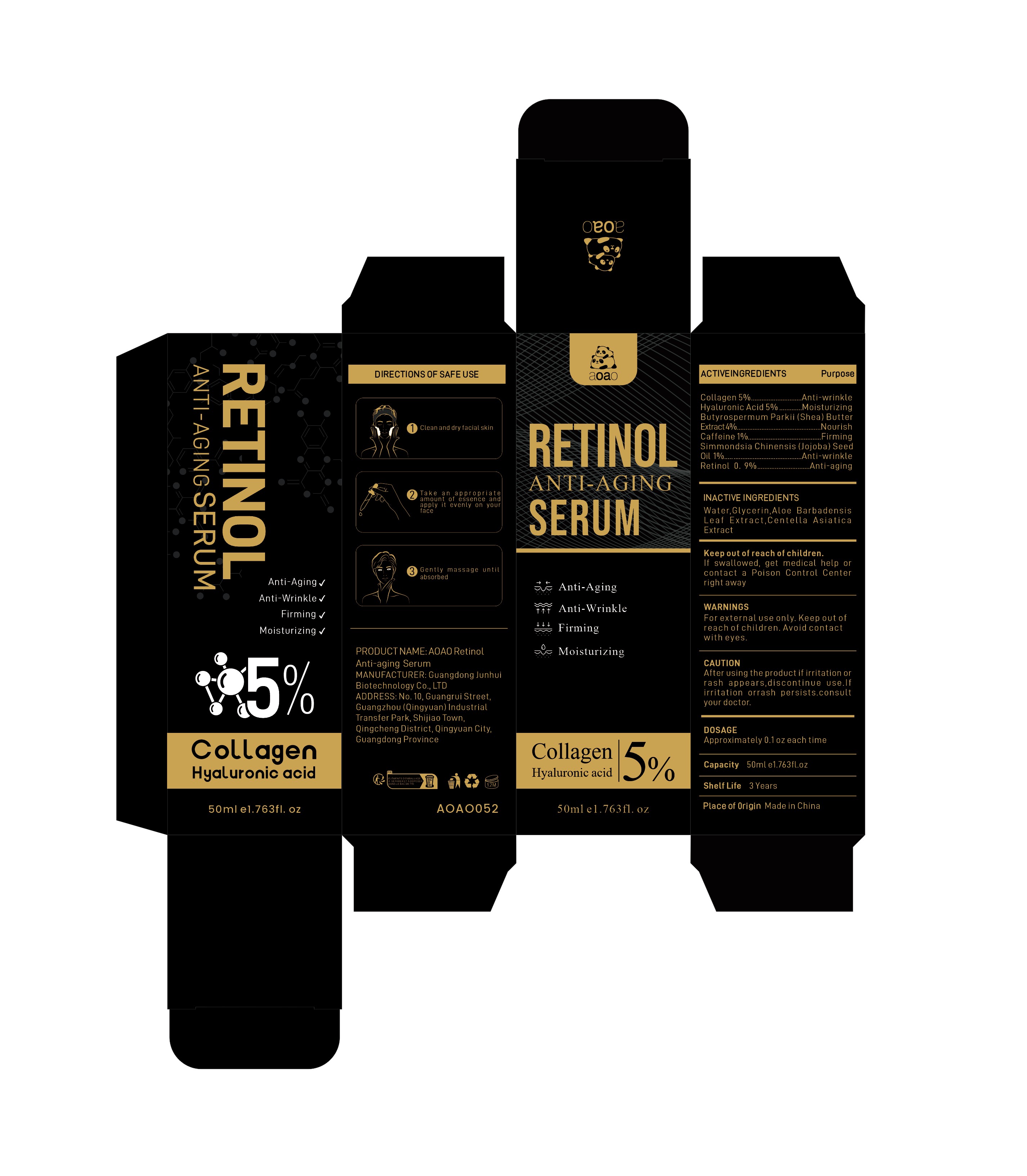 DRUG LABEL: AOAO Retinol Anti-aging Serum
NDC: 84509-048 | Form: LIQUID
Manufacturer: Guangdong Junhui Biotechnology Co., LTD
Category: otc | Type: HUMAN OTC DRUG LABEL
Date: 20241108

ACTIVE INGREDIENTS: RETINOL 450 mg/50 mL; HYALURONIC ACID 2500 mg/50 mL; CAFFEINE 500 mg/50 mL; COLLAGEN, SOLUBLE, FISH SKIN 2500 mg/50 mL; SIMMONDSIA CHINENSIS (JOJOBA) SEED OIL 500 mg/50 mL; BUTYROSPERMUM PARKII (SHEA) BUTTER EXTRACT 2000 mg/50 mL
INACTIVE INGREDIENTS: ALOE BARBADENSIS LEAF EXTRACT; WATER; GLYCERIN; CENTELLA ASIATICA TRITERPENOIDS

Active Ingredients

Collagen 5%
Butyrospermum Parkii (Shea) Butter Extract 4%
Hyaluronic Acid 5%
Caffeine 1%
Simmondsia Chinensis (Jojoba) Seed Oil 1%
Retinol 0.9%

Purpose

Anti-wrinkle
Nourish
Moisturizing
Firming
Anti-aging

Warnings

For external use only. Keep out ofreach of children.Avoid contact with eyes

Keep out of reach of children

If swallowed, get medical help or contact a Poison Control Center right away

CAUTION

After using the product if irritation or rash appears,discontinue use.If irritation or
rash persists.consult your doctor.

Uses

1. After cleansing, use a dropper to drop 3-5 drops of essence on the palm of your hand (applicable before or after toner)
2. Apply evenly on the face and neck, and gently massage until fully moisturized
3. The essence does not need to be washed off, and subsequent skin care steps can be performed after it is fully absorbed

Inactive Ingredients

Water,Glycerin，Aloe Barbadensis Leaf Extract，Centella Asiatica Extract

DOSAGE

Approximately 0.1fl.oz each time

Manufacturer

Guangdong Junhui Biotechnology Co., LTD

ADDRESS

No. 10, Guangrui Street, Guangzhou (Qingyuan) Industrial Transfer Park, Shijiao Town, Qingcheng District, Qingyuan City, Guangdong Province

Capacity

50ml e1.763fl.oz

Product Name

AOAO Retinol Anti-aging Serum

Shelf Life

3 Years

Place of Origin

Made in China